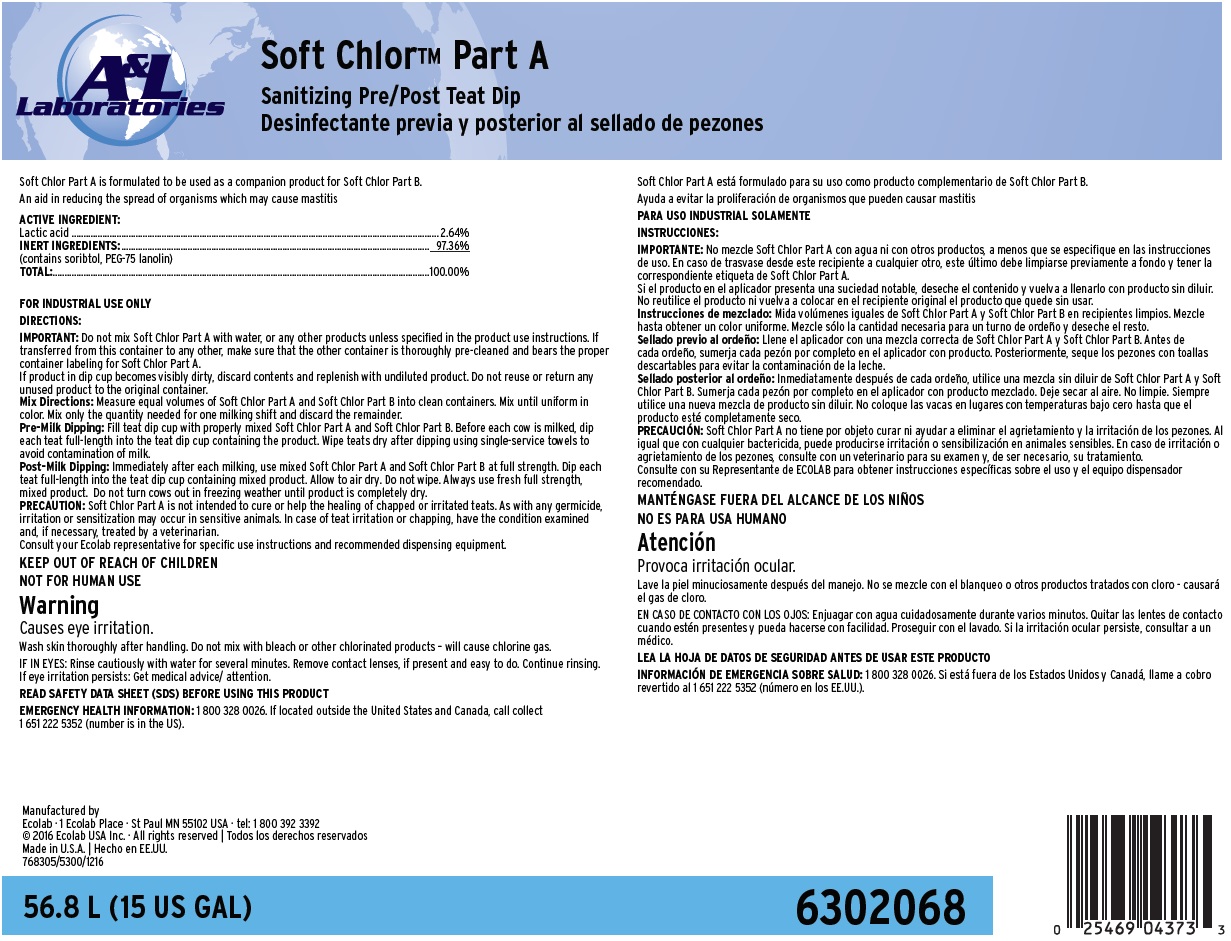 DRUG LABEL: Soft Tuch
NDC: 47593-544 | Form: SOLUTION
Manufacturer: Ecolab Inc.
Category: animal | Type: OTC ANIMAL DRUG LABEL
Date: 20250929

ACTIVE INGREDIENTS: BRONOPOL 2 mg/1 mL
INACTIVE INGREDIENTS: GLYCERIN; PEG-75 LANOLIN; WATER

SAFE HANDLING WARNING

FOR INDUSTRIAL USE ONLY

KEEP OUT OF REACH OF CHILDREN

NOT FOR HUMAN USE

Wash hands thoroughly after handling. Get medical advice/attention if you feel unwell.

DIRECTIONS:

IMPORTANT: Do not further dilute with water or mix with any other teat dips. If product in dip cup becomes visibly dirty, discard contents and replenish with fresh product. Do not reuse or return any unused product to the original container.

Udder Prep: When using an udder wash step before milking, make sure to wash teats with appropriate udder wash solution using proper cleaning procedures. Teats should then be dried with single-service towels.

Directions for Teat Dipping

Pre-Milk Dipping: Before each cow is milked, and using fresh Soft Tuch, dip each teat full-length into the teat dip cup. Wipe teats after dipping using single-service towels to avoid contamination of milk.

Post-Milk Dipping: Using fresh Soft Tuch, dip each teat full-length into the teat dip cup. Do not wipe. Allow to air dry. Do not turn cows out in freezing weather until the product is completely dry.

Expanded Usage: When freshening cows, begin dipping teats twice daily for about 10 days before calving. PRECAUTION: Soft Tuch is not intended to cure or help the healing of chapped or irritated teats. As with any germicide, irritation or sensitization may occur in sensitive animals. In case of teat irritation or chapping, have the condition examined and, if necessary, treated by a veterinarian.

Consult your Ecolab representative for speciﬁc use instructions and recommended dispensing equipment.

OTHER SAFETY INFORMATION

FIRST AID

IN CASE OF EYE CONTACT: Rinse with plenty of water.

IN CASE OF SKIN CONTACT: Rinse with water.

IF SWALLOWED: Rinse mouth. Get medical attention if symptoms occur.

IF INHALED: Get medical attention if symptoms occur.

READ SAFETY DATA SHEET (SDS) BEFORE USING THIS PRODUCT

EMERGENCY HEALTH INFORMATION: 1 800 328 0026. If located outside the United States and Canada, call collect 1 651 222 5352 (number is in the US).

Representative label and principal display panel

A&L Laboratories

Soft Tuch™

Non-Iodine Barrier Teat Dip

An aid in reducing the spread of organisms which may cause mastitis

ACTIVE INGREDIENT:

Bronopol................................................................................ 0.2%

SKIN CONDITIONING SYSTEM:

(contains glycerin and lanolin)....................................... 9.0%

INERT INGREDIENTS:.......................................... 90.8%

TOTAL:.......................................................................................... 100.0%

NET CONTENTS: 56.8 L (15 US GAL)

6301452

Manufactured by

Ecolab Inc. · 370 Wabasha Street N · St Paul MN 55102-1390 USA · tel: 1 800 392 3392

© 2015 Ecolab USA Inc. · All rights reserved

Made in United States

761190/5300/0315